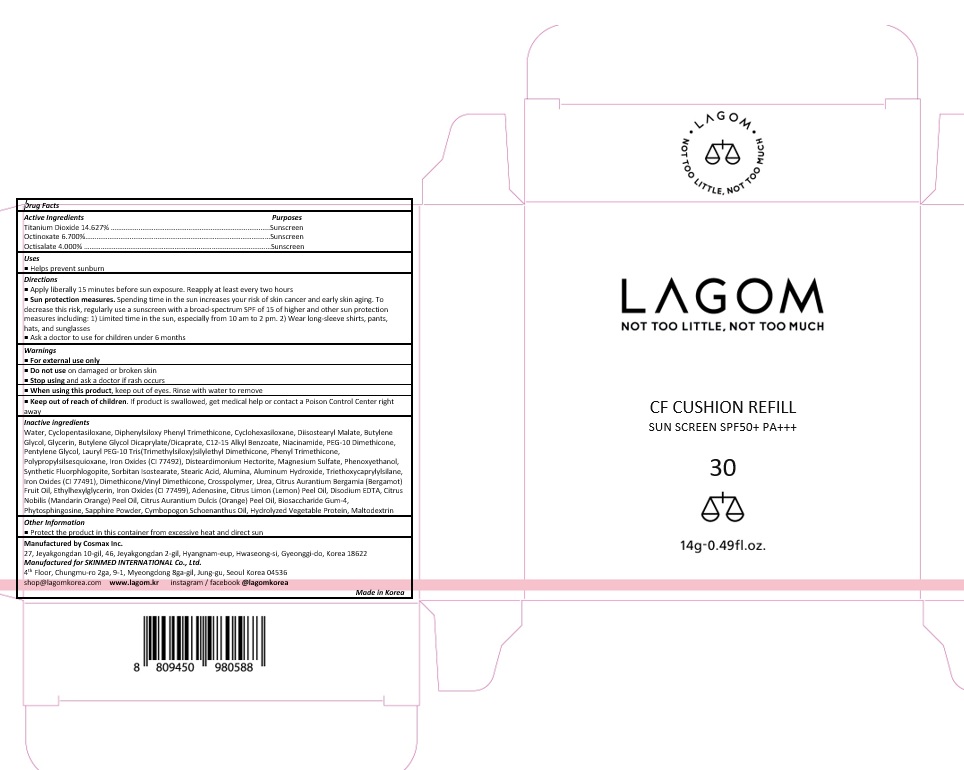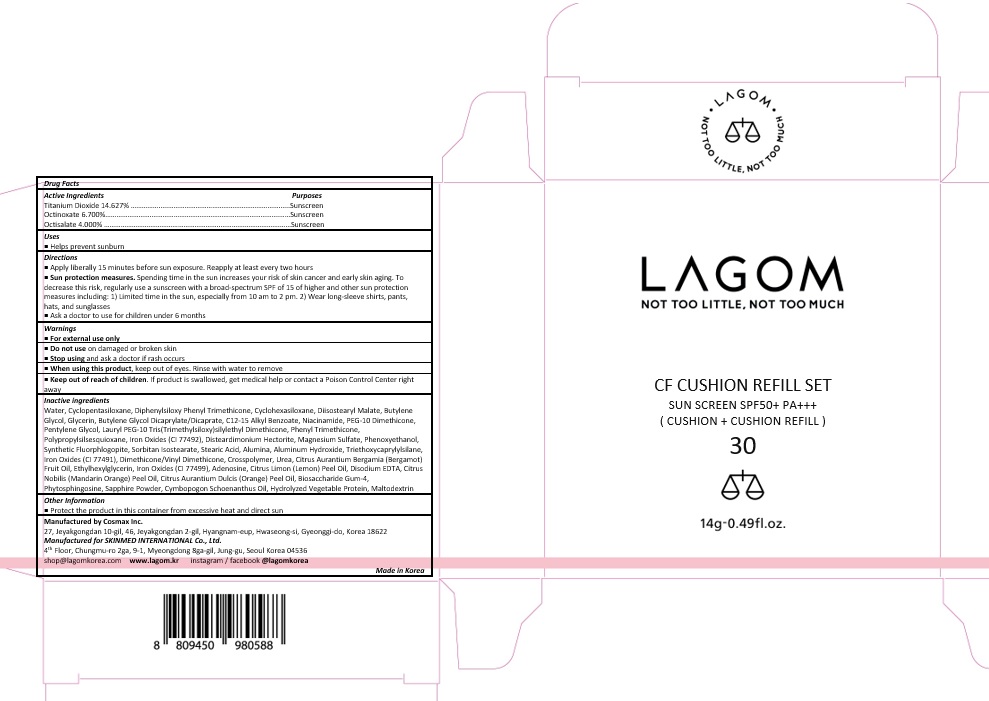 DRUG LABEL: Lagom CF Cushion 30
NDC: 70738-005 | Form: CREAM
Manufacturer: SKINMED International Co., Ltd.
Category: otc | Type: HUMAN OTC DRUG LABEL
Date: 20191023

ACTIVE INGREDIENTS: TITANIUM DIOXIDE 0.1462 g/1 g; OCTINOXATE 0.067 g/1 g; OCTISALATE 0.04 g/1 g
INACTIVE INGREDIENTS: WATER; CYCLOMETHICONE 5; DIPHENYLSILOXY PHENYL TRIMETHICONE; CYCLOMETHICONE 6; DIISOSTEARYL MALATE; BUTYLENE GLYCOL; GLYCERIN; BUTYLENE GLYCOL DICAPRYLATE/DICAPRATE; ALKYL (C12-15) BENZOATE; NIACINAMIDE; PEG-10 DIMETHICONE (600 CST); PENTYLENE GLYCOL; PHENYL TRIMETHICONE; FERRIC OXIDE YELLOW; DISTEARDIMONIUM HECTORITE; MAGNESIUM SULFATE, UNSPECIFIED FORM; PHENOXYETHANOL; SORBITAN ISOSTEARATE; STEARIC ACID; ALUMINUM OXIDE; ALUMINUM HYDROXIDE; TRIETHOXYCAPRYLYLSILANE; FERROSOFERRIC OXIDE; DIMETHICONE/VINYL DIMETHICONE CROSSPOLYMER (HARD PARTICLE); UREA; BERGAMOT OIL; ETHYLHEXYLGLYCERIN; ADENOSINE; LEMON OIL; EDETATE DISODIUM ANHYDROUS; MANDARIN OIL; ORANGE OIL; BIOSACCHARIDE GUM-4; PHYTOSPHINGOSINE; CYMBOPOGON SCHOENANTHUS OIL; MALTODEXTRIN

70738-005_V3

ACTIVE INGREDIENT

Titanium Dioxide 14.627%

Octinoxate 6.700%

Octisalate 4.000%

PURPOSE

Sunscreen

INDICATIONS AND USAGE

Helps prevent sunburn

DOSAGE AND ADMINISTRATION

Apply liberally 15 minutes before sun exposure. Reapply at least every two hours

Sun protection measures. Spending time in the sun increases your risk of skin cancer and early skin aging. To decrease this risk, regularly use a sunscreen with a broad spectrum SPF of 15 of higher and other sun protection measures including: 1) Limited time in the sun, especially from 10 am to 2 pm. 2) Wear long-sleeve shirts, pants, hats, and sunglasses

Ask a doctor to use for children under 6 months

WARNINGS

For external use only.
Do not use on damaged or broken skin.
When using this product, keep out of eyes. Rinse with water to remove.
Stop using and ask a doctor if rash occurs.

KEEP OUT OF REACH OF CHILDREN

Keep out of reach of the children. If product is swallowed, get medical help or contact a poison control center right away.

INACTIVE INGREDIENT

Water, Cyclopentasiloxane, Diphenylsiloxy Phenyl Trimethicone, Cyclohexasiloxane, Diisostearyl Malate, Butylene Glycol, Glycerin, Butylene Glycol Dicaprylate/Dicaprate, C12-15 Alkyl Benzoate, Niacinamide, PEG-10 Dimethicone, Pentylene Glycol, Lauryl PEG-10 Tris(Trimethylsiloxy)silylethyl Dimethicone, Phenyl Trimethicone, Polypropylsilsesquioxane, Iron Oxides (CI 77492), Disteardimonium Hectorite, Magnesium Sulfate, Phenoxyethanol, Synthetic Fluorphlogopite, Sorbitan Isostearate, Stearic Acid, Alumina, Aluminum Hydroxide, Triethoxycaprylylsilane, Iron Oxides (CI 77491), Dimethicone/Vinyl Dimethicone, Crosspolymer, Urea, Citrus Aurantium Bergamia (Bergamot) Fruit Oil, Ethylhexylglycerin, Iron Oxides (CI 77499), Adenosine, Citrus Limon (Lemon) Peel Oil, Disodium EDTA, Citrus Nobilis (Mandarin Orange) Peel Oil, Citrus Aurantium Dulcis (Orange) Peel Oil, Biosaccharide Gum-4, Phytosphingosine, Sapphire Powder, Cymbopogon Schoenanthus Oil, Hydrolyzed Vegetable Protein, Maltodextrin